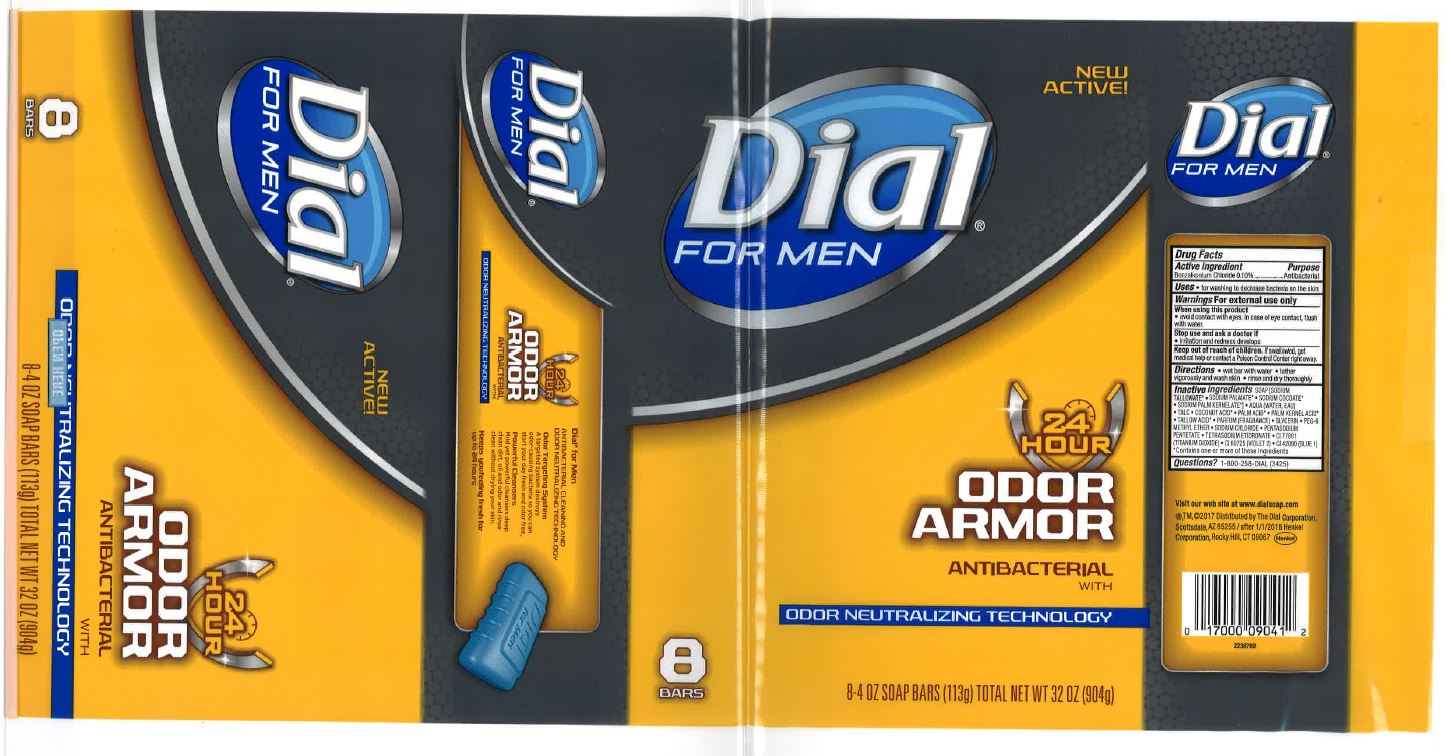 DRUG LABEL: Dial Antibacterial Bar
NDC: 54340-275 | Form: SOAP
Manufacturer: The Dial Corporation, A Henkel Company
Category: otc | Type: HUMAN OTC DRUG LABEL
Date: 20170825

ACTIVE INGREDIENTS: BENZALKONIUM CHLORIDE 0.1 g/100 g
INACTIVE INGREDIENTS: SODIUM TALLOWATE, BEEF 59.1 g/100 g

Dial for men odor armor

Active Ingredient

Benzalkonium Chloride 0.1%

Purpose

Antibacterial

Uses

for washing to decrease the bacteria on the skin.

Warning

For external use only.

When using this product avoid contact with eyes. In case of eye contact, flush with water.

Stop using and ask doctor if irritation or redness develops.

Keep out of reach of children

If swallowed, get medical help or contact Poison Control Center right away.

Directions

wet bar with water

lather vigorously and wash skin

rinse and dry thoroughly

Inactive Ingredient

Soap [Sodium Tallowate*, Sodium Palmate*, Sodium Cocoate*, Sodium Palm Kernelate*], Aqua (Water, Eau), Talc, Coconut Acid*, Palm Acid*, Palm Kernel Acid*, Tallow Acid*, Glycerin, PEG-6 Methyl Ether, Parfum(Fragrance), Sodium Chloride, Pentasodium Pentetate, Tetrasodium Etidronate, CI 77891 (Titanium Dioxide), CI 60725 (Violet 2), CI 42090 (Blue 1), *Contains one or more of these ingredients